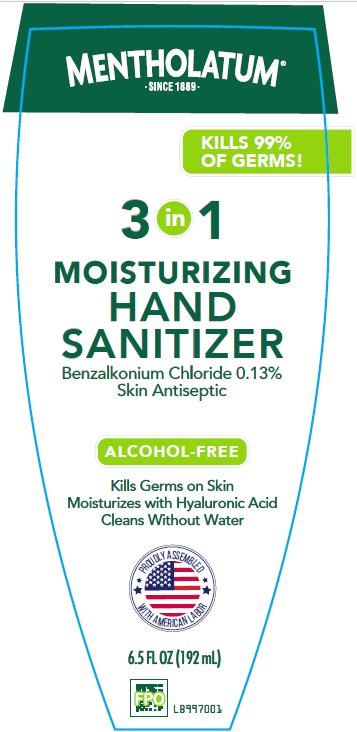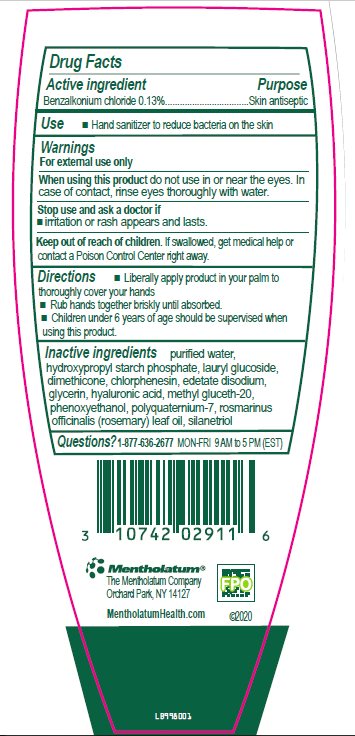 DRUG LABEL: Mentholatum Moisturizing Hand Sanitizer
NDC: 10742-0004 | Form: GEL
Manufacturer: The Mentholatum Company
Category: otc | Type: HUMAN OTC DRUG LABEL
Date: 20241213

ACTIVE INGREDIENTS: BENZALKONIUM CHLORIDE 1.3 mg/1 mL
INACTIVE INGREDIENTS: WATER; HYDROXYPROPYL DISTARCH PHOSPHATE, HIGH AMYLOSE CORN; LAURYL GLUCOSIDE; DIMETHICONE; CHLORPHENESIN; EDETATE DISODIUM; GLYCERIN; HYALURONIC ACID; METHYL GLUCETH-20; PHENOXYETHANOL; POLYQUATERNIUM-7 (70/30 ACRYLAMIDE/DADMAC; 1600000 MW); ROSEMARY OIL; SILANETRIOL

Drug Facts - Mentholatum Moisturizing Hand Sanitizer

Active ingredients

Benzalkonium Chloride 0.13%

Purpose

Skin antiseptic

Uses

- Hand sanitizer to reduce bacteria on the skin

Warnings

For external use only

When using this product

- do not use in or near the eyes. In case of contact, rinse eyes thoroughly with water.

Stop use and ask a doctor if

- irritation or rash appears and lasts.

Directions

- Liberally apply product in your palm to thoroughly cover your hands
- Rub hands together briskly until absorbed.
- Children under 6 years of age should be supervised when using this product.

Inactive ingredients

purified water, hydroxypropyl starch phosphate, lauryl glucoside, dimethicone, chlorphenesin, edetate disodium, glycerin, hyaluronic acid, methyl gluceth-20, phenoxyethanol, polyquaternium-7, rosmarinus officinalis (rosemary) leaf oil, silanetriol

Questions?

1-877-636-2677 MON-FRI 9 AM to 5 PM (EST)